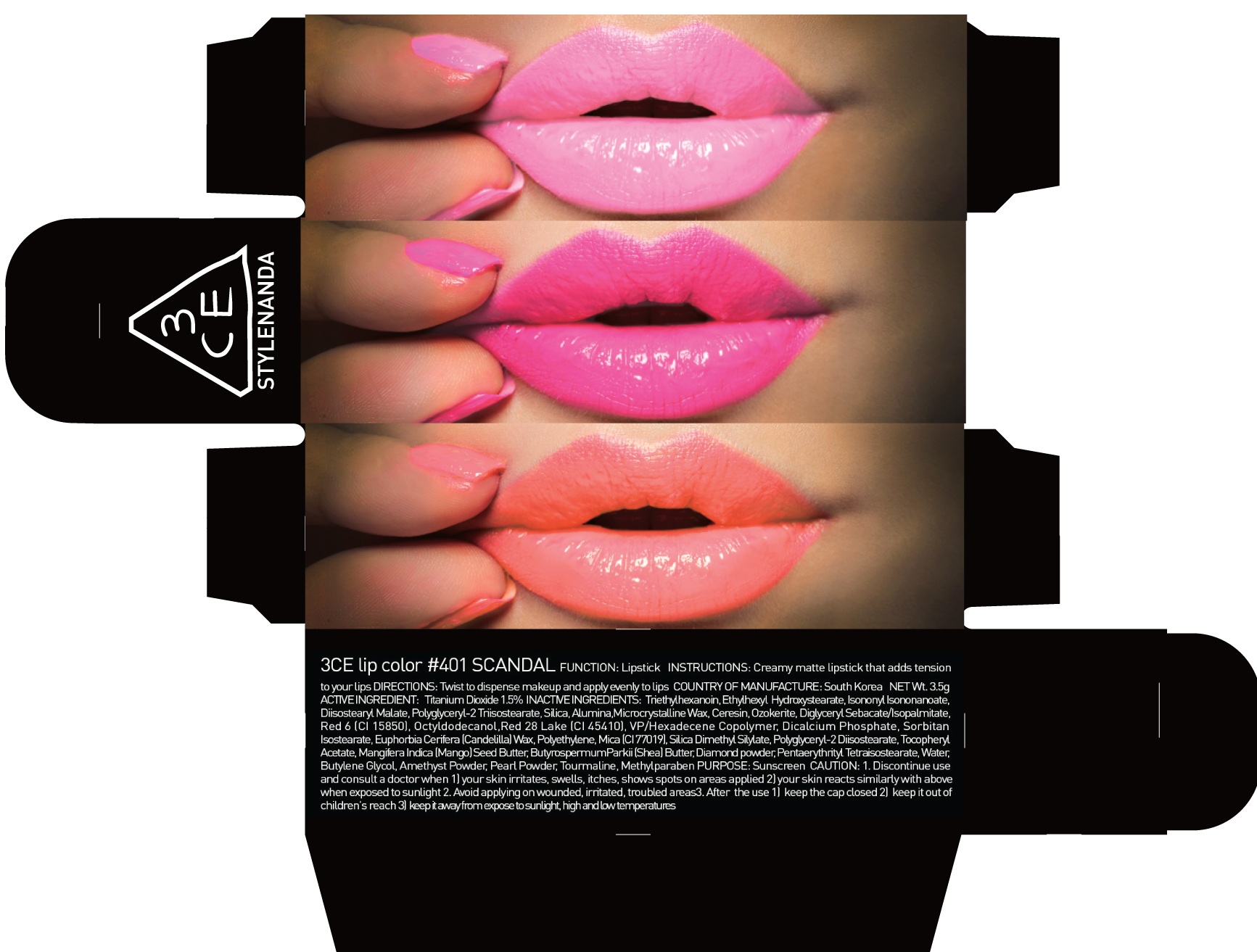 DRUG LABEL: 3CE LIP COLOR 401 SCANDAL
NDC: 60764-069 | Form: LIPSTICK
Manufacturer: Nanda Co., Ltd
Category: otc | Type: HUMAN OTC DRUG LABEL
Date: 20161005

ACTIVE INGREDIENTS: Titanium Dioxide 0.05 g/3.5 g
INACTIVE INGREDIENTS: Triethylhexanoin; Isononyl Isononanoate

ACTIVE INGREDIENT

Active Ingredient: Titanium Dioxide 1.5%

INACTIVE INGREDIENT

Inactive Ingredients: Triethylhexanoin, Polyglyceryl-2 Triisostearate, Trimethylolpropane Tricaprylate/Tricaprate, Isononyl Isononanoate, Mica (CI 77019), Diisostearyl Malate, Diglyceryl Sebacate/Isopalmitate, Silica, Ceresin, Ozokerite, Vinyl Dimethicone/Methicone Silsesquioxane Crosspolymer, Pentaerythrityl Tetraisostearate, Red 6 (CI 15850), Red 28 Lake (CI 45410), VP/Hexadecene Copolymer, Microcrystalline Wax, Sorbitan Isostearate, Silica Silylate, Polyethylene, Synthetic Wax, Silica Dimethyl Silylate, Polyglyceryl-2 Diisostearate, Methicone, Ethylene/Propylene Copolymer, Cholesteryl Macadamiate, Methylparaben, Mangifera Indica (Mango) Seed Butter, Butyrospermum Parkii (Shea) Butter, Water, Butylene Glycol, Diamond powder, Amethyst Powder, Pearl Powder, Tourmaline

PURPOSE

Purpose: Sunscreen

CAUTION

CAUTION: 1. Discontinue use and consult a doctor when - your skin irritates, swells, itches, shows spots on areas applied - your skin reacts similarly with above when exposed to sunlight 2. Avoid applying on wounded, irritated, troubled areas 3. After the use - keep the cap closed - keep it out of children's reach - keep it away from expose to sunlight, high and low temperatures

DESCRIPTION

INSTRUCTIONS: A rich color lipstick that moistly adheres to lips.

Directions: Twist to dispense makeup and apply evenly to lips